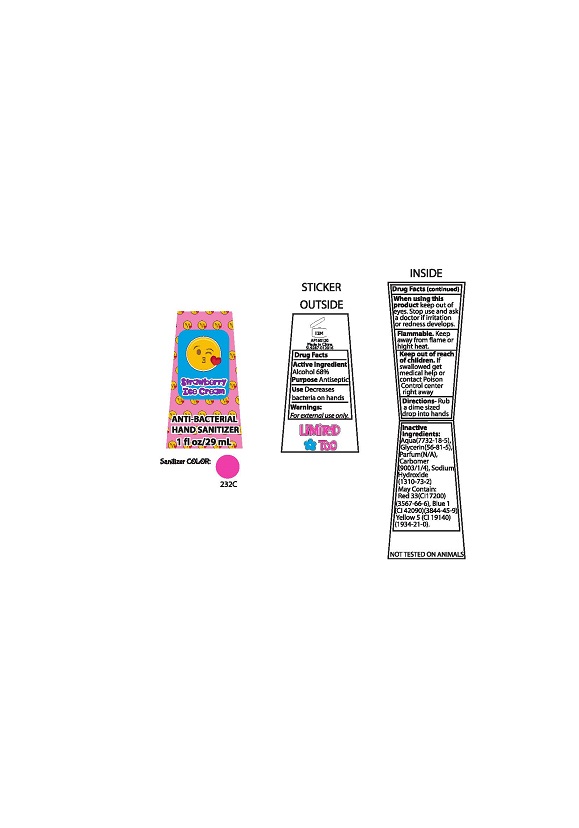 DRUG LABEL: Strawberry Ice cream Anti-Bacterial Hand Sanitizer
NDC: 54860-028 | Form: GEL
Manufacturer: SHENZHEN LANTERN SCIENCE CO., LTD
Category: otc | Type: HUMAN OTC DRUG LABEL
Date: 20160520

ACTIVE INGREDIENTS: ALCOHOL 68 mL/100 mL
INACTIVE INGREDIENTS: CARBOMER 1342; GLYCERIN; SODIUM HYDROXIDE; WATER

PURPOSE

Antibacterial

To decrease bacteria on skin

ACTIVE INGREDIENT

Alcohol ....68%

DOSAGE AND ADMINISTRATION

Rub a dime sized drop into hands

WARNINGS

For external use only - hands.

Keep out of eyes.

Stop use and contact a doctor if irritation or redness develops.

Flamable - keep away from flame or high heat.

KEEP OUT OF REACH OF CHILDREN

If swallowed get medical help or poison control right away.

INDICATIONS AND USAGE

To decrease bacteria on skin that could cause disease.

INACTIVE INGREDIENTS

WATER (AQUA/EAU)
GLYCERIN
CARBOMER
FRAGRANCE (PARFUM)
SODIUM HYDROXIDE